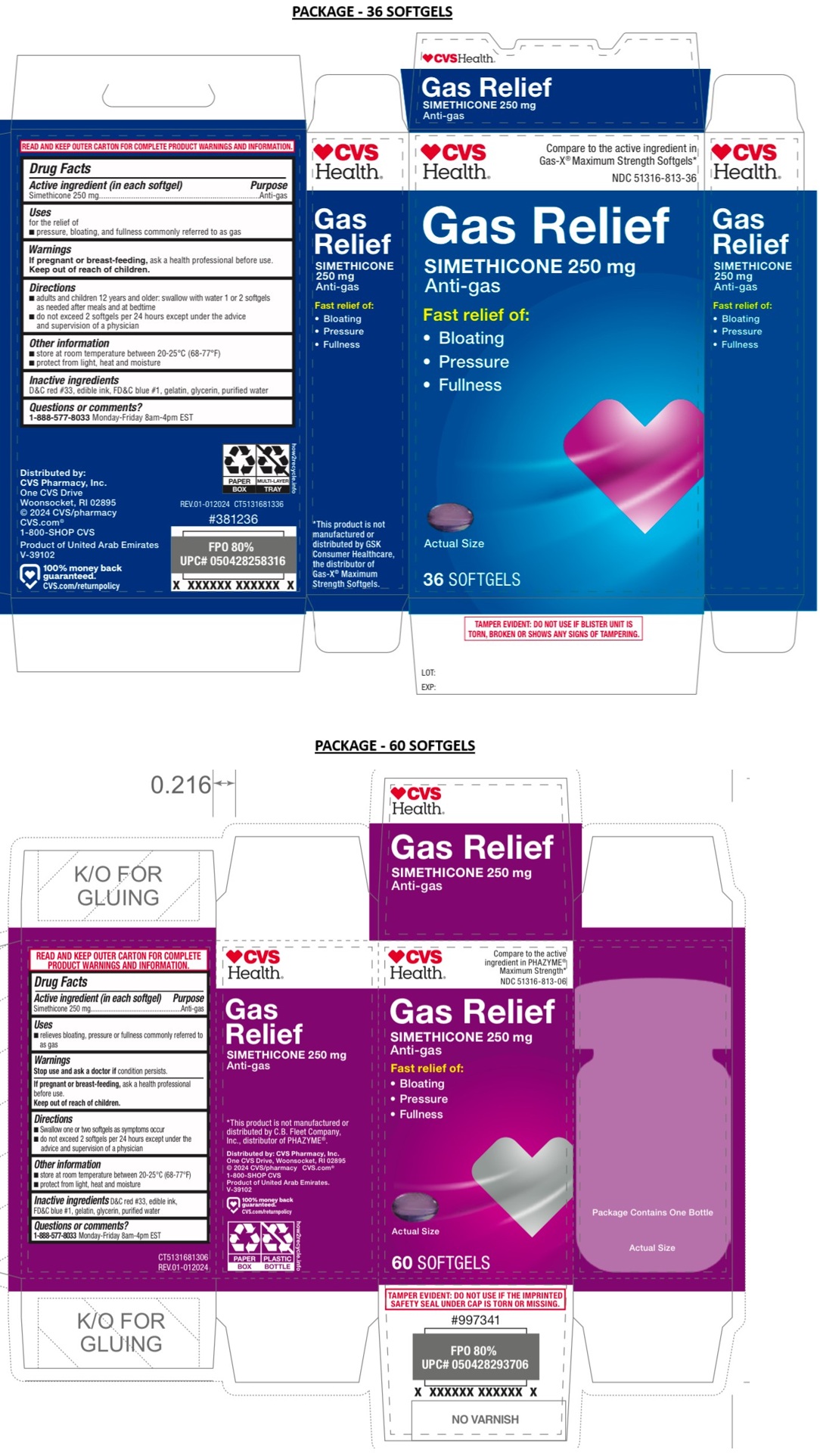 DRUG LABEL: Maximum Strength Gas Relief Softgel
NDC: 51316-813 | Form: CAPSULE, LIQUID FILLED
Manufacturer: CVS PHARMACY, INC
Category: otc | Type: HUMAN OTC DRUG LABEL
Date: 20241230

ACTIVE INGREDIENTS: DIMETHICONE, UNSPECIFIED 250 mg/1 1
INACTIVE INGREDIENTS: D&C RED NO. 33; FD&C BLUE NO. 1; GELATIN, UNSPECIFIED; GLYCERIN; WATER

Maximum Strength Gas Relief Softgel

Active ingredient (in each softgel)

Simethicone 250 mg

Purpose

Anti-gas

Uses

• relieves bloating, pressure or fullness commonly referred to as gas

Warnings

Stop use and ask a doctor if condition persists.

If pregnant or breast-feeding, ask a health professional before use.

Keep out of reach of children.

Directions

• Swallow one or two softgels as symptoms occur
• do not exceed 2 softgels per 24 hours except under the advice and supervision of a physician

Other information

• store at room temperature 20-25°C (68-77°F)
• protect from light, heat and moisture

Inactive ingredients

D&C red #33, edible ink, FD&C blue #1, gelatin, glycerin, purified water

Questions or comments?

1-888-577-8033 Monday-Friday 8am-4pm EST

Compare to the active ingredient in Gas-X® Maximum Strength Softgels*

*This product is not manufactured or distributed by GSK Consumer Healthcare, the distributor of Gas-X® Maximum Strength Softgels.

Compare to the active ingredient in PHAZYME® Maximum Strength*

Fast relief of:
• Bloating
• Pressure
• Fullness

READ AND KEEP OUTER CARTON FOR COMPLETE PRODUCT WARNINGS AND INFORMATION.

TAMPER EVIDENT: DO NOT USE IF THE IMPRINTED SAFETY SEAL UNDER CAP IS TORN OR MISSING.

*This product is not manufactured or distributed by C.B. Fleet Company, Inc., distributor of PHAZYME®.

Distributed by: CVS Pharmacy, Inc.
One CVS Drive, Woonsocket, RI 02895
© 2022 CVS/pharmacy CVS.com®
1-800-SHOP CVS
Product of United Arab Emirates.
V-39102